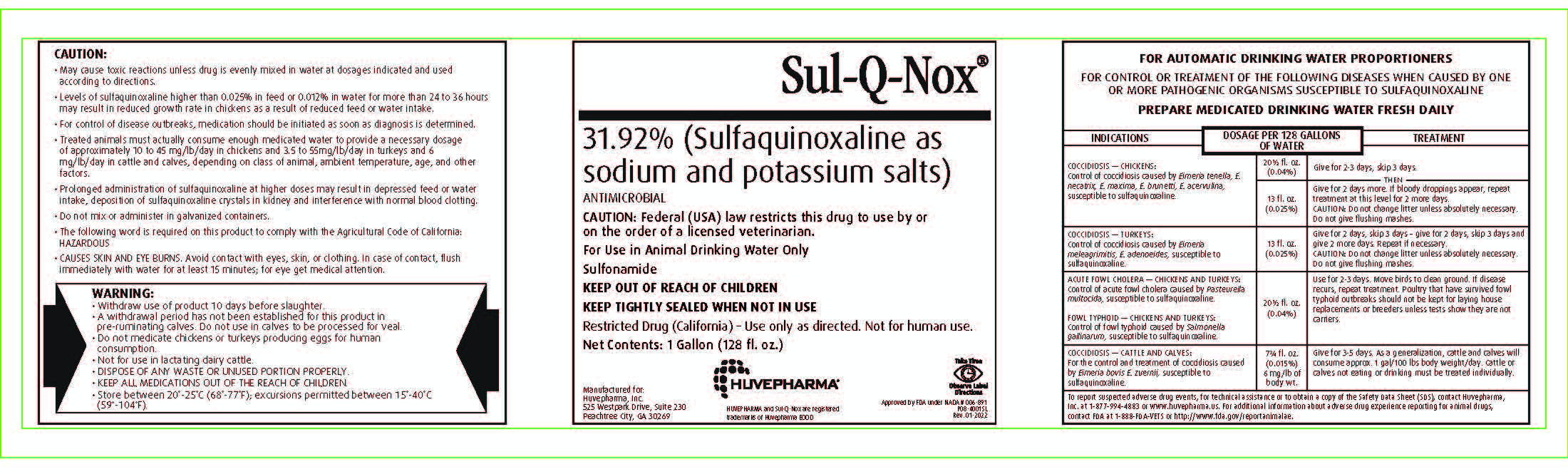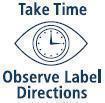 DRUG LABEL: Sul-Q-Nox
NDC: 23243-6771 | Form: Solution
Manufacturer: Huvepharma, Inc
Category: animal | Type: PRESCRIPTION ANIMAL DRUG LABEL
Date: 20231005

ACTIVE INGREDIENTS: SULFAQUINOXALINE .3192 g/1 mL

Sul-Q-Nox®

31.92% (Sulfaquinoxaline as sodium and potassium salts)

ANTIMICROBIAL

PRECAUTIONS

Caution: Federal (USA) law restricts this drug to use by or on the
order of a licensed veterinarian.
For Use in Animal Drinking Water Only
Sulfonamide

KEEP OUT OF REACH OF CHILDREN
KEEP TIGHTLY SEALED WHEN NOT IN USE

Restricted Drug (California) - Use only as directed. Not for human use.

Net Contents: 1 Gallon (128 fl. oz.)

Manufactured for:
Huvepharma, Inc.
525 Westpark Drive, Suite 230
Peachtree City, GA 30269

HUVEPHARMA®

HUVEPHARMA and Sul-Q-Nox are registered
trademarks of Huvepharma EOOD

Approved by FDA under NADA # 006-891
P08-4001SL
Rev. 01-2022

GENERAL PRECAUTIONS

CAUTION:

• May cause toxic reactions unless drug is evenly mixed in water at dosages indicated and used according
to directions.
• Levels of sulfaquinoxaline higher than 0.025% in feed or 0.012% in water for more than 24 to 36 hours
may result in reduced growth rate in chickens as a result of reduced feed or water intake.
• For control of disease outbreaks, medication should be initiated as soon as diagnosis is determined.
• Treated animals must actually consume enough medicated water to provide a necessary dosage of
approximately 10 to 45 mg/lb/day in chickens and 3.5 to 55 mg/lb/day in turkeys and 6 mg/lb/day in
cattle and calves, depending on class of animal, ambient temperature, age, and other factors.
• Prolonged administration of sulfaquinoxaline at higher doses may result in depressed feed or water
intake, deposition of sulfaquinoxaline crystals in kidney and interference with normal blood clotting.
• Do not mix or administer in galvanized containers.
• The follwing word is required on this product to comply with Agricultural Code of California:
HAZARDOUS
• CAUSES SKIN AND EYE BURNS. Avoid contact with eyes, skin, or clothing. In case of contact, flush
immediately with water for at least 15 minutes; for eye get medical attention.

WARNING:

• Withdraw use of product 10 days before slaughter.
• A withdrawal period has not been established for this product in pre-ruminating
calves. Do not use in calves to be processed for veal.
• Do not medicate chickens or turkeys producing eggs for human
consumption.
• Not for use in lactating dairy cattle.
• DISPOSE OF ANY WASTE OR UNUSED PORTION PROPERLY.
• KEEP ALL MEDICATIONS OUT OF THE REACH OF CHILDREN.
• Store between 20°- 25°C (68°- 77°F); excursions permitted between
15°- 40°C (59°- 104°F).

INDICATIONS AND USAGE

FOR AUTOMATIC DRINKING WATER PROPORTIONERS
FOR CONTROL OR TREATMENT OF THE FOLLOWING DISEASES WHEN CAUSED BY ONE
OR MORE PATHOGENIC ORGANISMS SUSCEPTIBLE TO SULFAQUINOXALINE
PREPARE MEDICATED DRINKING WATER FRESH DAILY

INDICATIONS | DOSAGE PER 128 GALLONS OF WATER | TREATMENT
COCCIDIOSIS — CHICKENS: Control of coccidiosis caused by Eimeria tenella, E. necatrix, E. maxima, E. brunetti, E. acervulina, susceptible to sulfaquinoxaline. | 20½ fl. oz. (0.04%) | Give for 2-3 days, skip 3 days.; Then
COCCIDIOSIS — CHICKENS: Control of coccidiosis caused by Eimeria tenella, E. necatrix, E. maxima, E. brunetti, E. acervulina, susceptible to sulfaquinoxaline. | 13 fl. oz. (0.025%) | Give for 2 days more. If bloody droppings appear, repeat treatment at this level for 2 more days. CAUTION: Do not change litter unless absolutely necessary. Do not give flushing mashes.
COCCIDIOSIS — TURKEYS: Control of coccidiosis caused by Eimeria meleagrimitis, E. adenoeides, susceptible to sulfaquinoxaline. | 13 fl. oz. (0.025%) | Give for 2 days - skip 3 days - give for 2 days - skip 3 days and give 2 more days. Repeat if necessary. CAUTION: Do not change litter unless absolutely necessary. Do not give flushing mashes.
ACUTE FOWL CHOLERA — CHICKENS AND TURKEYS: Control of acute fowl cholera caused by Pasteurella multocida susceptible to sulfaquinoxaline. FOWL TYPHOID — CHICKENS AND TURKEYS: Control of fowl typhoid caused by Salmonella gallinarum, susceptible to sulfaquinoxaline. | 20½ fl. oz. (0.04%) | Use for 2-3 days. Move birds to clean ground. If disease recurs, repeat treatment. Poultry that have survived fowl typhoid outbreaks should not be kept for laying house replacements or breeders unless tests show they are not carriers.
COCCIDIOSIS — CATTLE AND CALVES: For the control and treatment of coccidiosis caused by Eimeria bovis, E. zuernii, susceptible to sulfaquinoxaline. | 7¾ fl. oz. (0.015%) 6 mg/lb of body wt. | Give for 3-5 days. As a generalization, cattle and calves will consume approx. 1 gal/100 lbs body weight/day. Cattle or calves not eating or drinking must be treated; individually.
To report suspected adverse drug events, for technical assistance or to obtain a copy of the Safety Data Sheet (SDS), contact Huvepharma, Inc. at 1-877-994-4883 or www.huvepharma.us. For additional information about adverse drug experience reporting for animal drugs, contact FDA at 1-888-FDA-VETS or http://www.fda.gov/reportanimalae.